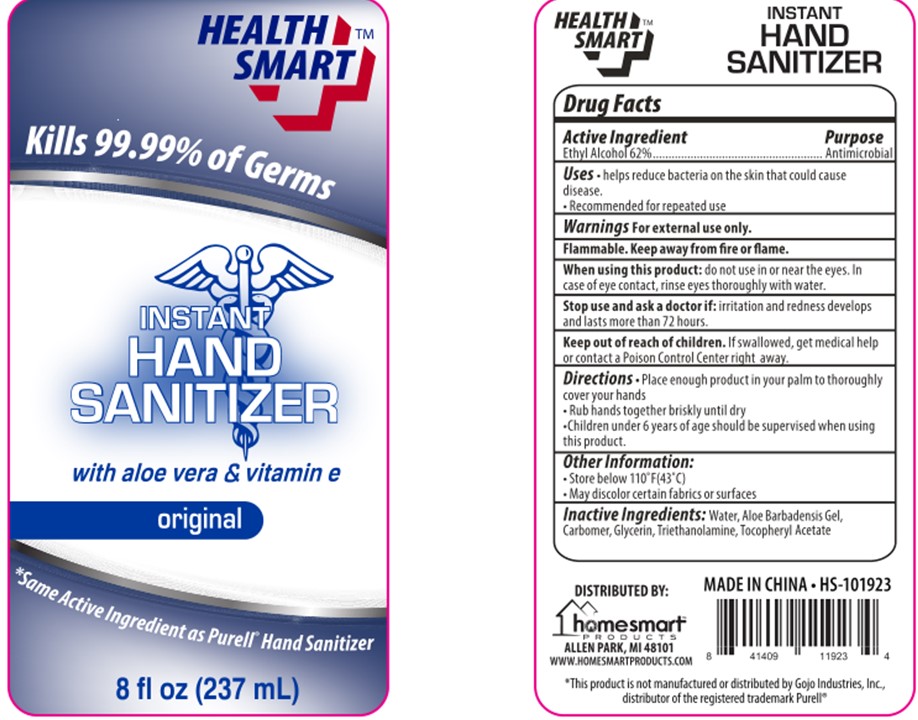 DRUG LABEL: HEALTH SMART HAND SANITIZER
NDC: 75749-018 | Form: GEL
Manufacturer: NINGBO PRETTY TOURISM MANUFACTURE CO.,LTD.
Category: otc | Type: HUMAN OTC DRUG LABEL
Date: 20200628

ACTIVE INGREDIENTS: ALCOHOL 62 mL/100 mL
INACTIVE INGREDIENTS: TROLAMINE; GLYCERIN; PROPYLENE GLYCOL; ALOE; WATER; CARBOMER HOMOPOLYMER, UNSPECIFIED TYPE; .ALPHA.-TOCOPHEROL ACETATE

ACTIVE INGREDIENT

Ethyl Alcohol 62%

Purpose

Antimicrobial

Uses

- helps reduce bacteria on the skin that could cause disease.
- Recommended for repeated use

Warnings

For external use only

Flammable

Keep away from fire or flame

When using this product: do not use in or near the eyes. In case of eye contact, rinse eyes thoroughly with water.

Stop use and ask a doctor if irritation and redness develops and lasts more than 72 hours.

Keep out of reach of children

if swallowed, get medical help or contact a Posion Control Center right away.

Directions

- Place enough product in your palm to thoroughly cover your hands
- Rub hands together briskly until dry
- Children under 6 years of age should be supervised when using this product.

Other information

- Store below 110F(43C)
- May discolor certain fabrics or surfaces

Inactive ingredients

Water

Aloe Barbadensis Gel

Carbomer

Glycerin

Triethanoloamine

Tocopheryl Acetate